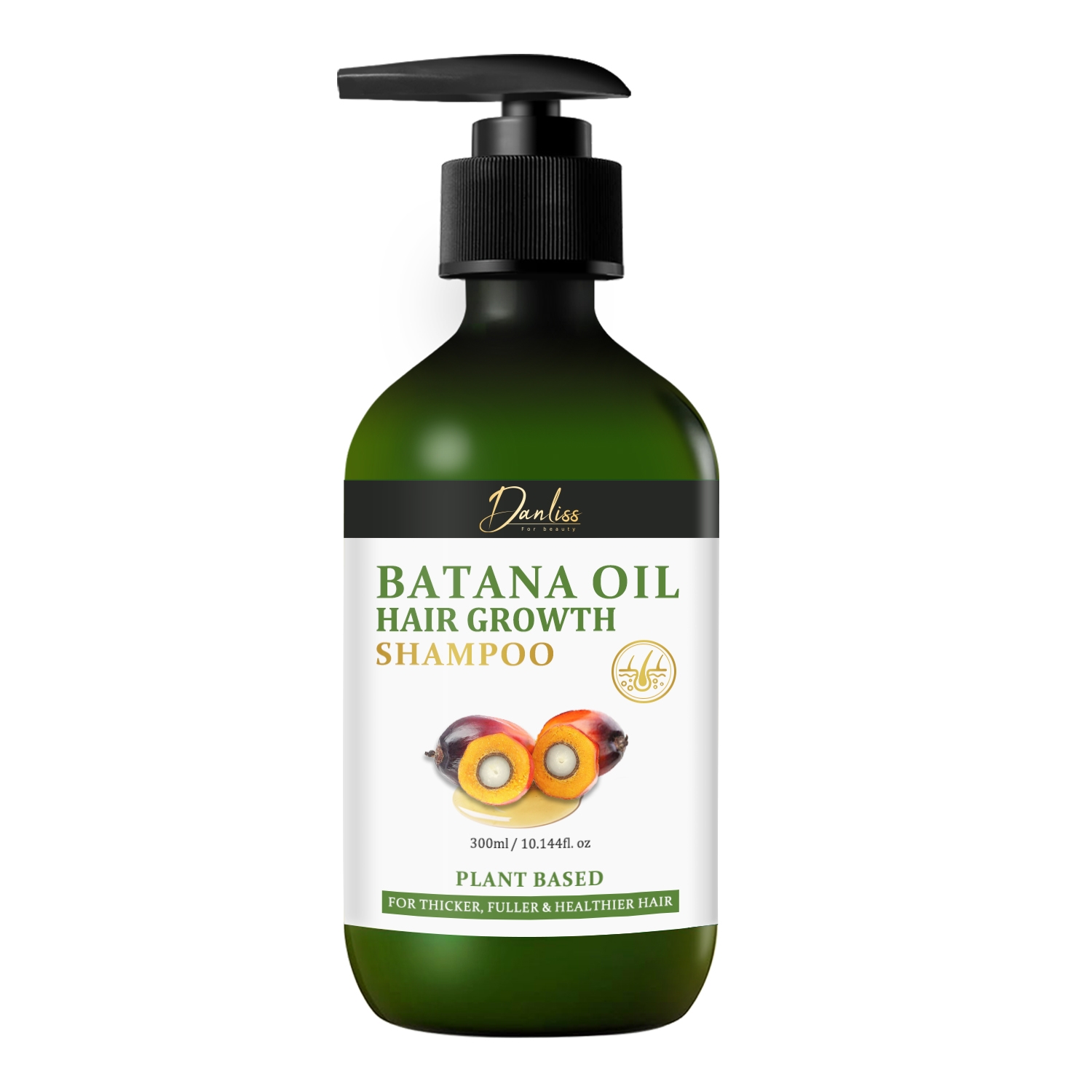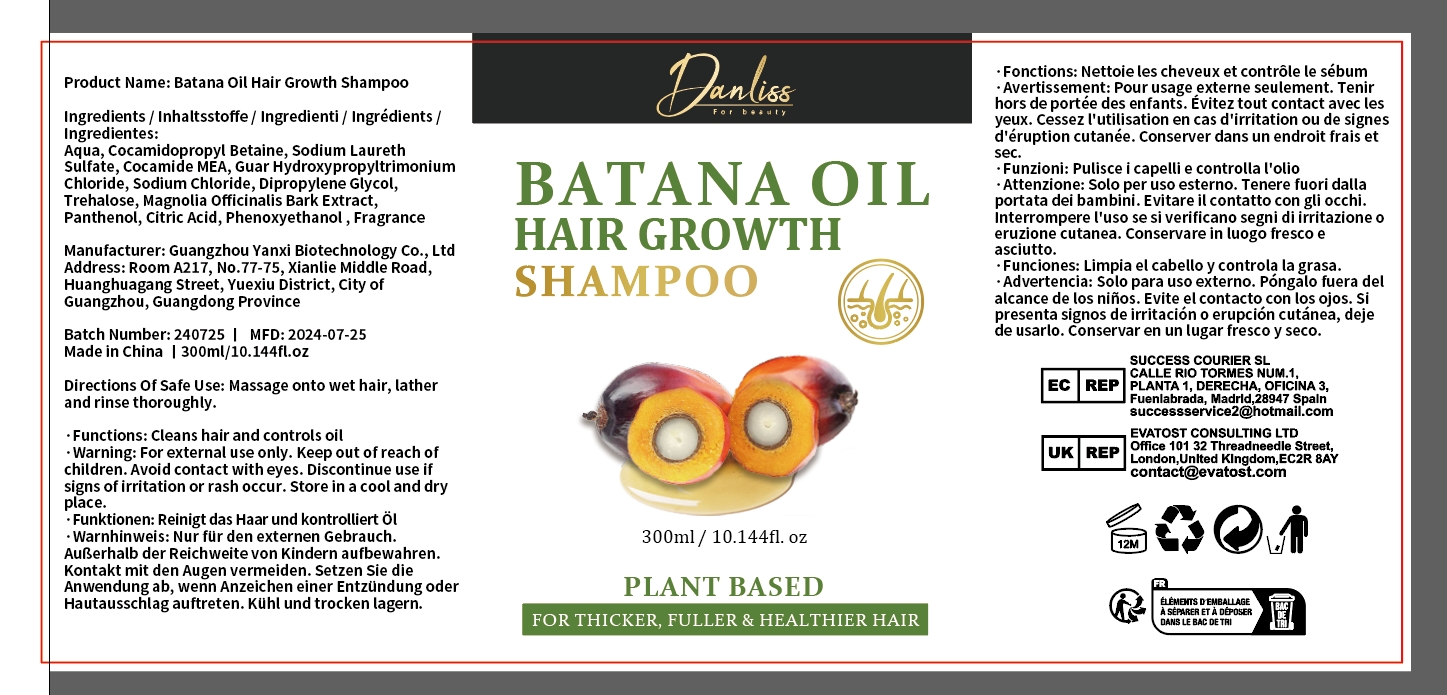 DRUG LABEL: Batana Oil HairGrowthShampoo
NDC: 84025-186 | Form: SHAMPOO
Manufacturer: Guangzhou Yanxi Biotechnology Co.. Ltd
Category: otc | Type: HUMAN OTC DRUG LABEL
Date: 20240912

ACTIVE INGREDIENTS: COCAMIDOPROPYL BETAINE 5 mg/300 mL; DIPROPYLENE GLYCOL 3 mg/300 mL
INACTIVE INGREDIENTS: WATER

DOSAGE AND ADMINISTRATION

Shampoo for healthy hair growth and smooth hair

WARNINGS

keep out of children

INACTIVE INGREDIENT

AQUA

INDICATIONS AND USAGE

For daily hair care

keep out of children

PURPOSE

Effectively nourishes the scalp and smoothes hair